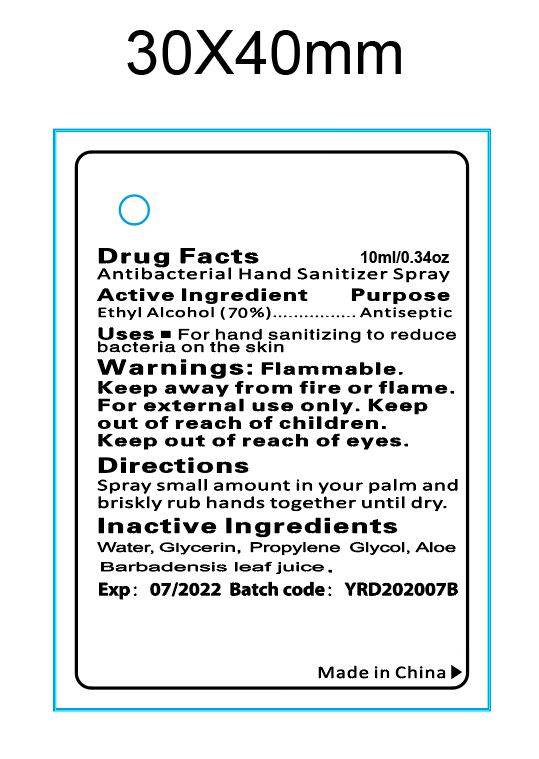 DRUG LABEL: ANTIBACTERIAL HAND SANITIZERSPRAY
NDC: 47993-314 | Form: LIQUID
Manufacturer: NINGBO JIANGBEI OCEAN STAR TRADING CO.,LTD
Category: otc | Type: HUMAN OTC DRUG LABEL
Date: 20201105

ACTIVE INGREDIENTS: ALCOHOL 70 g/112 mL
INACTIVE INGREDIENTS: WATER; GLYCERIN; PROPYLENE GLYCOL; ALOE VERA LEAF

47993-314

Active ingredients

Ethyl Alcohol (70%)

PURPOSE

Antiseptic

Uses：

- For hand sanitizing to reduce bacteria on the skin.

Warnings:

Flammable. Keep away from fire or flame.For external use only.

Keep out of reach of children.

WHEN USING

Keep out of reach of eyes.

Directions:

Squeeze small amount in your palm and briskly rub hands together until dry.

Inactive Ingredients:

Water,Glycerin,Propylene Glycol,Aloe Barbaensis Leaf Juice